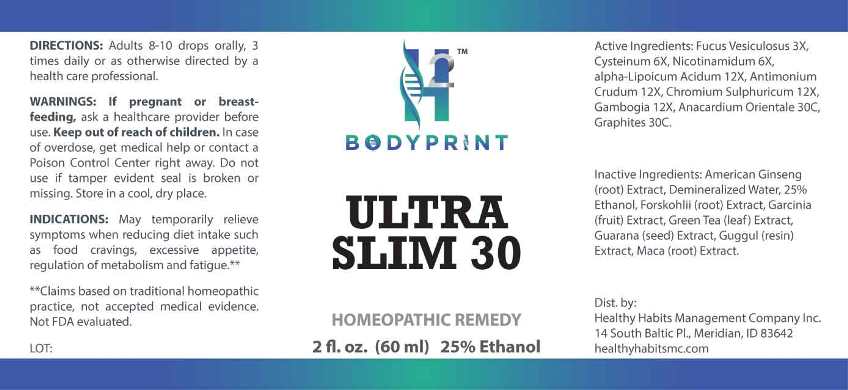 DRUG LABEL: Ultra Slim 30
NDC: 74550-0001 | Form: LIQUID
Manufacturer: Healthy Habits Management Company Inc.
Category: homeopathic | Type: HUMAN OTC DRUG LABEL
Date: 20260112

ACTIVE INGREDIENTS: FUCUS VESICULOSUS 3 [hp_X]/1 mL; CYSTEINE 6 [hp_X]/1 mL; NIACINAMIDE 6 [hp_X]/1 mL; ALPHA LIPOIC ACID 12 [hp_X]/1 mL; ANTIMONY TRISULFIDE 12 [hp_X]/1 mL; CHROMIC SULFATE PENTADECAHYDRATE 12 [hp_X]/1 mL; GAMBOGE 12 [hp_X]/1 mL; SEMECARPUS ANACARDIUM JUICE 30 [hp_C]/1 mL; GRAPHITE 30 [hp_C]/1 mL
INACTIVE INGREDIENTS: AMERICAN GINSENG; GREEN TEA LEAF; GARCINIA GUMMI-GUTTA FRUIT; PAULLINIA CUPANA SEED; LEPIDIUM MEYENII ROOT; PLECTRANTHUS BARBATUS ROOT; GUGGUL; WATER; ALCOHOL

Drug Facts:

ACTIVE INGREDIENTS:

Fucus Vesiculosus 3X, Cysteinum 6X, Nicotinamidum 6X, Alpha-Lipoicum Acidum 12X, Antimonium Crudum 12X, Chromium Sulphuricum 12X, Gambogia 12X, Anacardium Orientale 30C, Graphites 30C.

INDICATIONS:

May temporarily relieve symptoms when reducing diet intake such as food cravings, excessive appetite, regulation of metabolism and fatigue.**

**Claims based on traditional homeopathic practice, not accepted medical evidence. Not FDA evaluated.

WARNINGS:

If pregnant or breast-feeding, ask a health professional before use.

Keep out of reach of children. In case of overdose, get medical help or contact a Poison Control Center right away.

Do not use if tamper evident seal is broken or missing.

Store in a cool, dry place.

Keep out of reach of children. In case of overdose, get medical help or contact a Poison Control Center right away.

DIRECTIONS:

Adults 8-10 drops orally, 3 times daily or as otherwise directed by a health care professional.

INDICATIONS:

May temporarily relieve symptoms when reducing diet intake such as food cravings, excessive appetite, regulation of metabolism and fatigue.**

**Claims based on traditional homeopathic practice, not accepted medical evidence. Not FDA evaluated.

INACTIVE INGREDIENTS:

American Ginseng (root) Panax Quinquefolius, Demineralized Water, 25% Ethanol, Green Tea (leaf) Camellia Sinensis, Garcinia (fruit) Garcinia Cambogia, Guarana (seed) Paullinia Cupana, Maca (root) Lepidium Meyenii, Forskohlii (root) Plectranthus Barbatus, Guggul (resin) Commiphora Mukul

QUESTIONS:

Dist. by:

Healthy Habits Management Company Inc.

14 South Baltic Pl., Meridian, ID 83642

heathyhabitsmc.com

PACKAGE LABEL DISPLAY:

ULTRA SLIM 30

HOMEOPATHIC REMEDY

2 fl. oz. (60 ml)